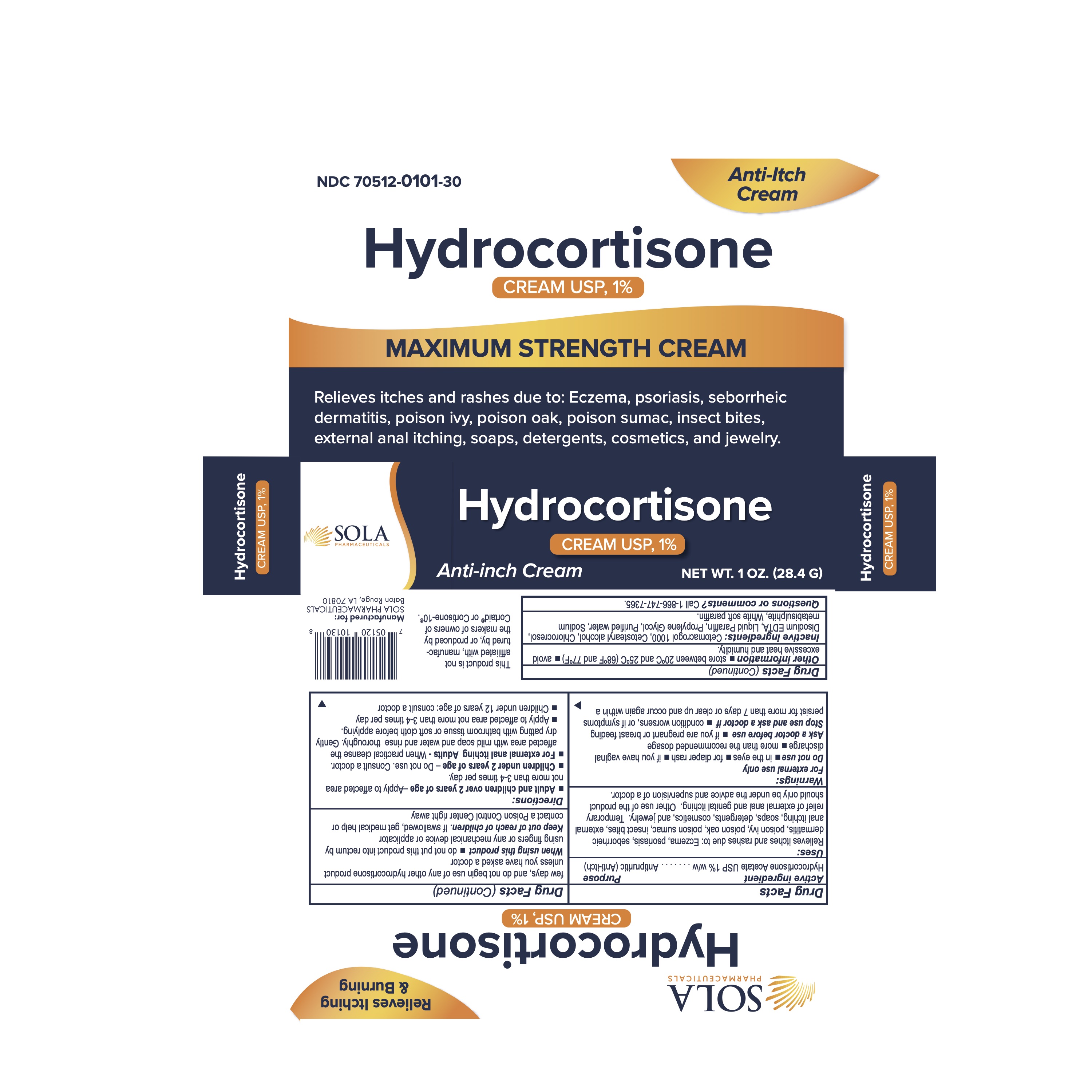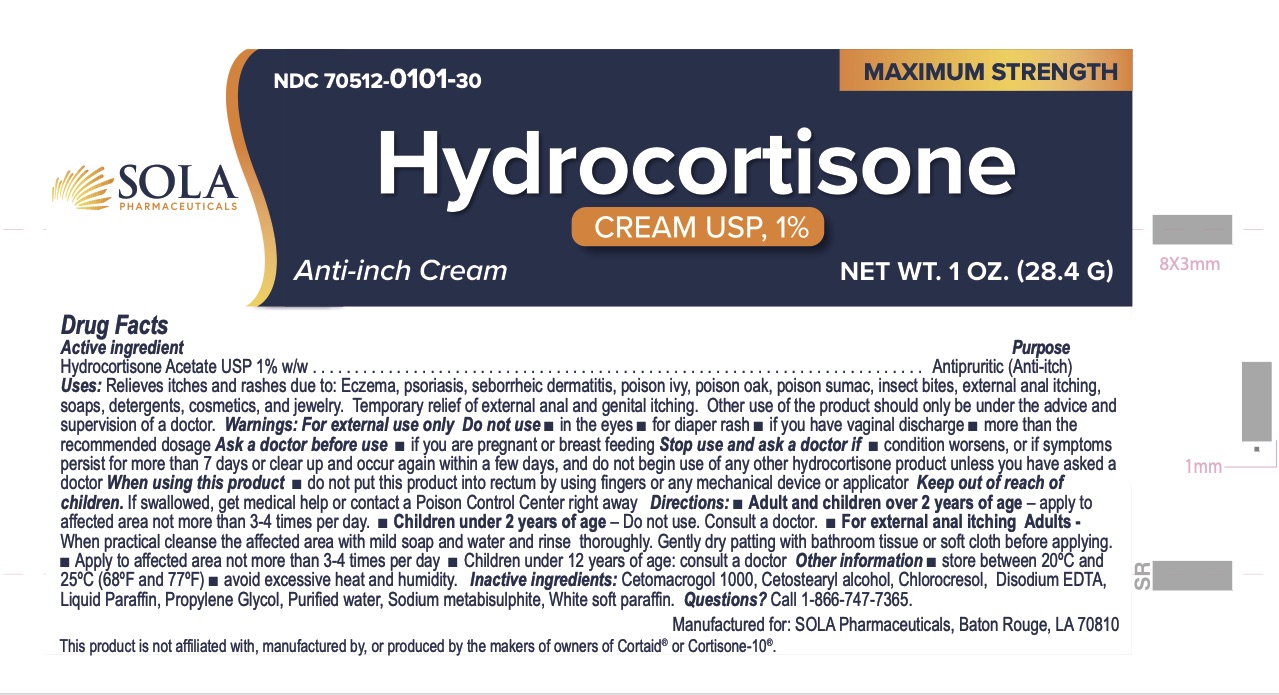 DRUG LABEL: Hydrocortisone Cream 1%
NDC: 70512-101 | Form: CREAM
Manufacturer: SOLA Pharmaceuticals
Category: otc | Type: HUMAN OTC DRUG LABEL
Date: 20220705

ACTIVE INGREDIENTS: HYDROCORTISONE 10 mg/1 g
INACTIVE INGREDIENTS: WATER; PETROLATUM; CETETH-20; DISODIUM EDTA-COPPER; CHLOROCRESOL; MINERAL OIL; PROPYLENE GLYCOL; SODIUM METABISULFITE; CETOSTEARYL ALCOHOL

Hydrocortisone Cream 1%

Active Ingredient

Hydrocortisone 1%

Purpose

Antipruritic (Anti-itch)

Uses

Relieves itches and rashes due to:

- Eczema
- Psoriasis
- Seborrheic dermatitis
- Poison ivy
- Poison oak
- Poison sumac
- Insect bites
- External anal itching
- Soaps
- Detergents
- Cosmetics
- Jewelry

Temporary relief of external anal and genital itching.

Other use of the product should only be under the advice and supervision of a doctor.

Warnings

For external use only

Do not use:

- In the eyes
- For diaper rash
- If you have vaginal discharge
- More than the recommended dosage

Ask doctor before use:

- If you are pregnant or breast feeding

Stop use and ask a doctor if:

- Condition worsens, or is symptoms persist for more than 7 days or clear up and occur again within a few days, and do not begin use of any other hydrocortisone product unless you have asked a doctor.

When using this product:

- Do not put this product into rectum by using fingers or any mechanical device or applicator.

Keep out of reach of children. If swallowed, get medical help or contact Poison Control Center right away

Directions

- Adults and children over 2 years of age - Apply to affected area not more than 3-4 times per day.
- Children under 2 years of age - Do not use. Consult a doctor.
  - For external anal itching Adults - When practical cleanse the affcted area with mild soap and water and rinse thoroughly. Gently dry patting with bathroom tissue or soft cloth before applying. Apply to affected area not more than 3-4 times per day. Children under 12 years of age: consult a doctor.

Other Information

- store between 20ºC and 25ºC (68ºFk and 77ºF)
- avoid excessive heat and humidity

Inactive Ingredients

Cetomacrogol 1000, Cetostearyl alcohol, Chlorocresol, Disodium EDTA, Liquid paraffin, Propylene glycol, Purified water, Sodium metabisulphite, White soft paraffin.

PACKAGE LABEL

Questions of comments? Call 1-866-747-7365

Manufactured for : SOLA Pharmaceuticals
Baton Rouge, LA 70810

Store in a dry, cool place

Hydrocortisone 1% Cream
NDC 70512-101-30

Qty: 28.4g